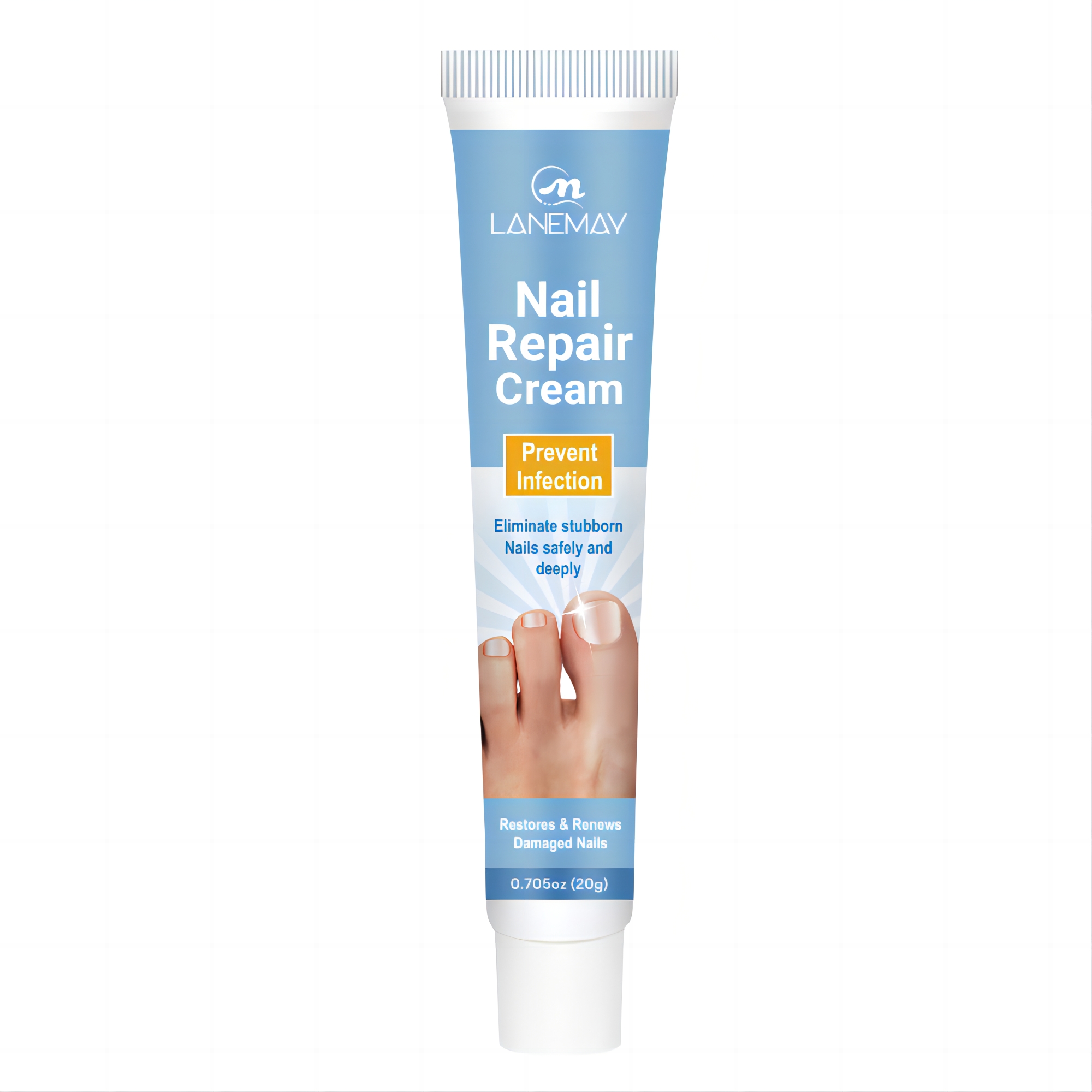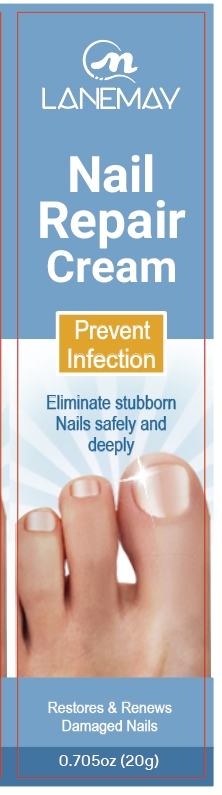 DRUG LABEL: Nail Repair Cream
NDC: 84025-060 | Form: PASTE
Manufacturer: Guangzhou Yanxi Biotechnology Co., Ltd
Category: otc | Type: HUMAN OTC DRUG LABEL
Date: 20240710

ACTIVE INGREDIENTS: HYDROGENATED AVOCADO OIL 2 mg/20 g; MINERAL OIL 3 mg/20 g
INACTIVE INGREDIENTS: WATER

DOSAGE AND ADMINISTRATION

USE AS A Nail Repair Cream

WARNINGS

keep out of children

INACTIVE INGREDIENT

Aqua

INDICATIONS AND USAGE

For restores and renews damaged Nails

keep out of children

PURPOSE

Eliminate stubborn nails safely and deeply